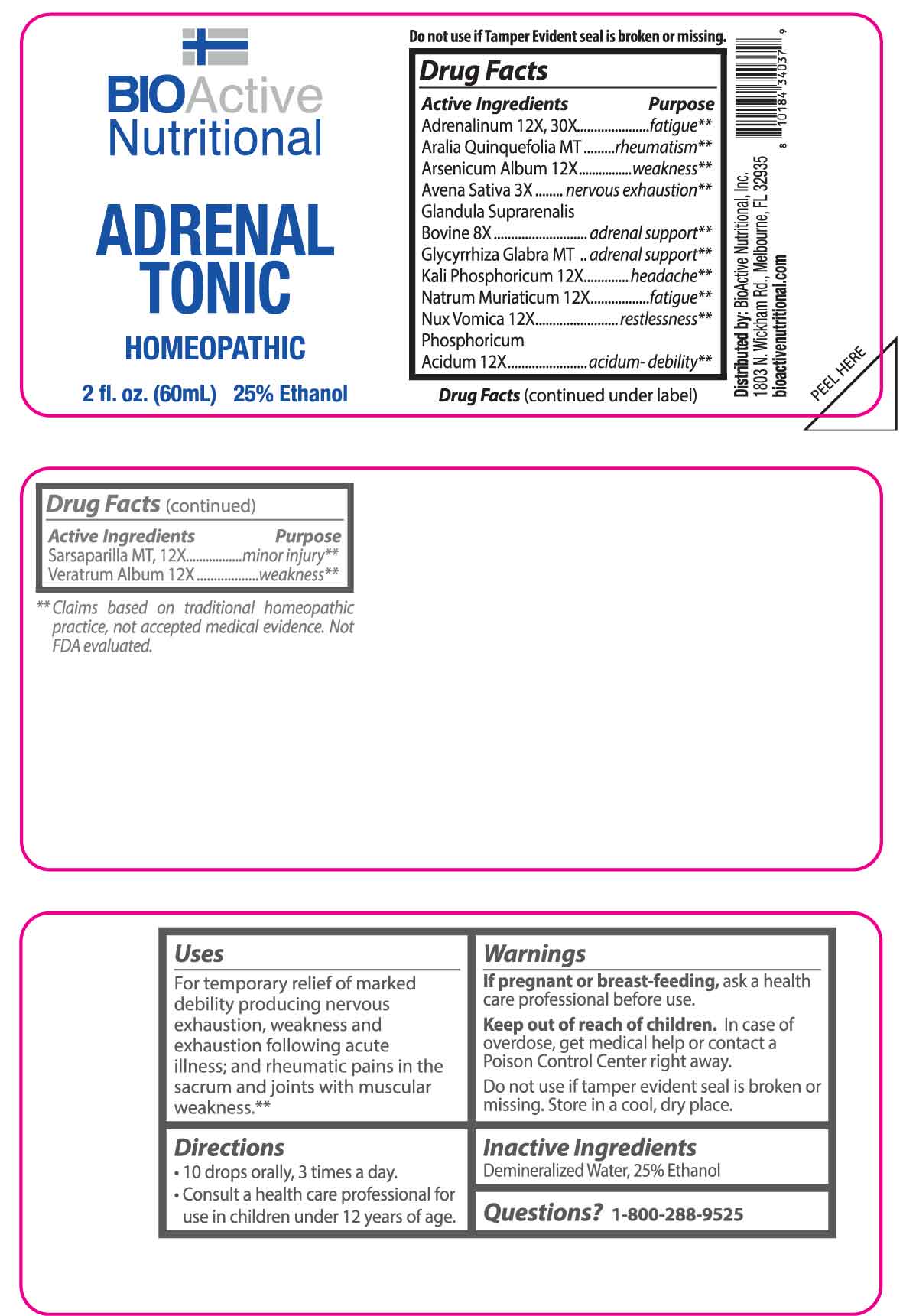 DRUG LABEL: Adrenal Tonic
NDC: 43857-0057 | Form: LIQUID
Manufacturer: BioActive Nutritional, Inc.
Category: homeopathic | Type: HUMAN OTC DRUG LABEL
Date: 20250520

ACTIVE INGREDIENTS: AMERICAN GINSENG 1 [hp_X]/1 mL; GLYCYRRHIZA GLABRA 1 [hp_X]/1 mL; SMILAX ORNATA ROOT 1 [hp_X]/1 mL; AVENA SATIVA FLOWERING TOP 3 [hp_X]/1 mL; BOS TAURUS ADRENAL GLAND 8 [hp_X]/1 mL; EPINEPHRINE 12 [hp_X]/1 mL; ARSENIC TRIOXIDE 12 [hp_X]/1 mL; POTASSIUM PHOSPHATE, DIBASIC 12 [hp_X]/1 mL; SODIUM CHLORIDE 12 [hp_X]/1 mL; STRYCHNOS NUX-VOMICA SEED 12 [hp_X]/1 mL; PHOSPHORIC ACID 12 [hp_X]/1 mL; VERATRUM ALBUM ROOT 12 [hp_X]/1 mL
INACTIVE INGREDIENTS: WATER; ALCOHOL

DRUG FACTS:

ACTIVE INGREDIENTS:

Adrenalinum 12X, 30X, Aralia Quinquefolia MT, Arsenicum Album 12X, Avena Sativa 3X, Glandula Suprarenalis Bovine 8X, Glycyrrhiza Glabra MT, Kali Phosphoricum 12X, Natrum Muriaticum 12X, Nux Vomica 12X, Phosphoricum Acidum 12X, Sarsaparilla MT, 12X, Veratrum Album 12X.

PURPOSE:

Adrenalinum - fatigue,** Aralia Quinquefolia - rheumatism,** Arsenicum Album - weakness,** Avena Sativa – nervous exhaustion,** Glandula Suprarenalis Bovine – adrenal support,** Glycyrrhiza Glabra – adrenal support,** Kali Phosphoricum - headache,** Natrum Muriaticum - fatigue,** Nux Vomica - restlessness,** Phosphoricum Acidum – Acidum debility,** Sarsaparilla – minor injury,** Veratrum Album – weakness**

**Claims based on traditional homeopathic practice, not accepted medical evidence. Not FDA evaluated.

USES:

For temporary relief of marked debility producing nervous exhaustion, weakness and exhaustion following acute illness; and rheumatic pains in the sacrum and joints with muscular weakness.**

**Claims based on traditional homeopathic practice, not accepted medical evidence. Not FDA evaluated.

WARNINGS:

If pregnant or breast-feeding, ask a health care professional before use.

Keep out of reach of children. In case of overdose, get medical help or contact a Poison Control Center right away.

Do not use if tamper evident seal is broken or missing.

Store in a cool, dry place.

KEEP OUT OF REACH OF CHILDREN:

In case of overdose, get medical help or contact a Poison Control Center right away.

DIRECTIONS:

• 10 drops orally, 3 times a day.

• Consult a health care professional for use in children under 12 years of age.

INACTIVE INGREDIENTS:

Demineralized Water, 25% Ethanol

QUESTIONS:

Distributed by:

BioActive Nutritional, Inc.

1803 N. Wickham Rd.

Melbourne, FL 32935

bioactivenutritional.com

1-800-288-9525

PACKAGE LABEL DISPLAY:

BIOActive Nutritional

ADRENAL TONIC

HOMEOPATHIC

2 fl. oz. (60mL)